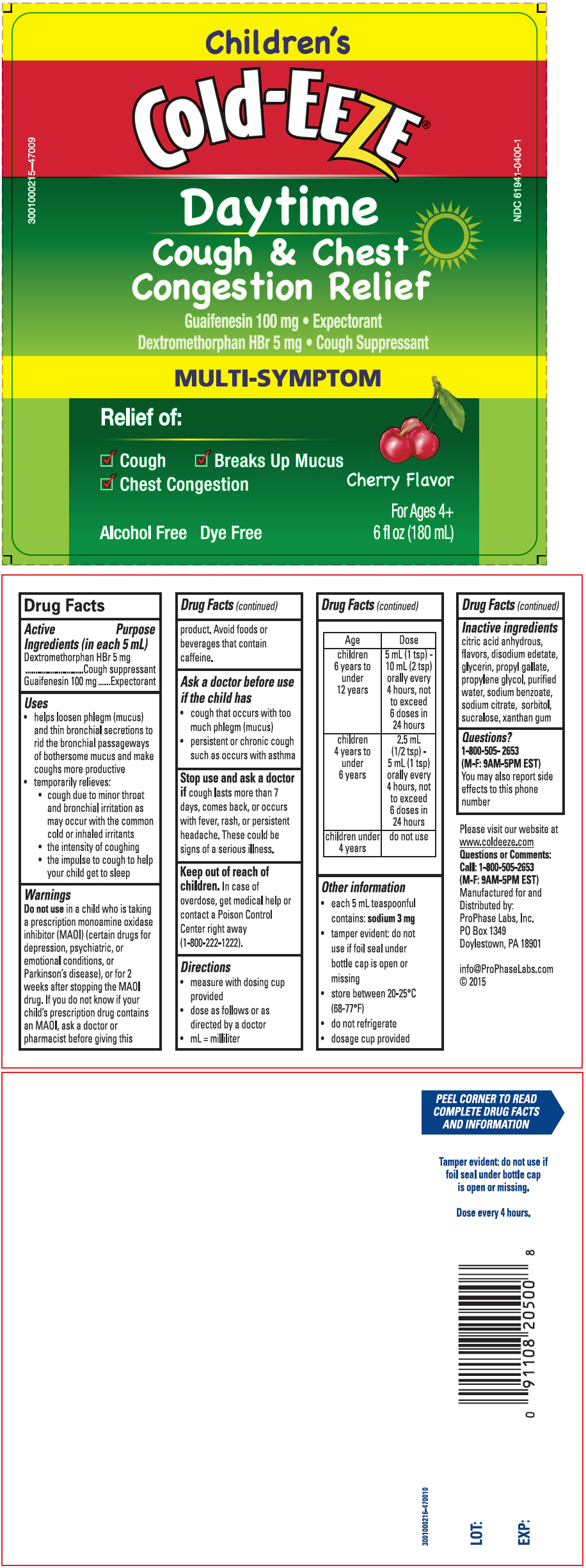 DRUG LABEL: Cold-EEZE 
NDC: 61941-0400 | Form: LIQUID
Manufacturer: ProPhase Labs, Inc.
Category: otc | Type: HUMAN OTC DRUG LABEL
Date: 20160129

ACTIVE INGREDIENTS: Dextromethorphan Hydrobromide 20 mg/5 mL; Guaifenesin 400 mg/5 mL
INACTIVE INGREDIENTS: Anhydrous Citric Acid; Edetate Disodium; Glycerin; Propylene Glycol; Water; Propyl Gallate; Sodium Benzoate; Sodium Citrate, Unspecified Form; Sorbitol; Sucralose; Xanthan Gum

Cold-EEZE®
Children's Daytime Cough & Chest Congestion Relief

Drug Facts

ACTIVE INGREDIENT

Active Ingredients (in each 5 mL) | Purpose
Dextromethorphan HBr 5 mg | Cough suppressant
Guaifenesin 100 mg | Expectorant

Uses

- helps loosen phlegm (mucus) and thin bronchial secretions to rid the bronchial passageways of bothersome mucus and make coughs more productive
- temporarily relieves:
  - cough due to minor throat and bronchial irritation as may occur with the common cold or inhaled irritants
  - the intensity of coughing
  - the impulse to cough to help your child get to sleep

Warnings

Do not use in a child who is taking a prescription monoamine oxidase inhibitor (MAOI) (certain drugs for depression, psychiatric, or emotional conditions, or Parkinson's disease), or for 2 weeks after stopping the MAOI drug. If you do not know if your child's prescription drug contains an MAOI, ask a doctor or pharmacist before giving this product. Avoid foods or beverages that contain caffeine.

Ask a doctor before use if the child has

- cough that occurs with too much phlegm (mucus)
- persistent or chronic cough such as occurs with asthma

Stop use and ask a doctor if cough lasts more than 7 days, comes back, or occurs with fever, rash, or persistent headache. These could be signs of a serious illness.

Keep out of reach of children. In case of overdose, get medical help or contact a Poison Control Center right away (1-800-222-1222).

Directions

- measure with dosing cup provided
- dose as follows or as directed by a doctor
- mL = milliliter

Age | Dose
children 6 years to under 12 years | 5 mL (1 tsp) - 10 mL (2 tsp) orally every 4 hours, not to exceed 6 doses in 24 hours
children 4 years to under 6 years | 2.5 mL (1/2 tsp) - 5 mL (1 tsp) orally every 4 hours, not to exceed 6 doses in 24 hours
children under 4 years | do not use

Other information

- each 5 mL teaspoonful contains: sodium 3 mg
- tamper evident: do not use if foil seal under bottle cap is open or missing
- store between 20-25°C (68-77°F)
- do not refrigerate
- dosing cup provided

Inactive ingredients

citric acid anhydrous, flavors, disodium edetate, glycerin, propyl gallate, propylene glycol, purified water, sodium benzoate, sodium citrate, sorbitol, sucralose, xanthan gum

Questions?

1-800-505-2653
(M-F: 9AM-5PM EST)
You may also report side effects to this phone number

Distributed by:
ProPhase Labs, Inc.
PO Box 1349
Doylestown, PA 18901

PRINCIPAL DISPLAY PANEL - 180 mL Bottle Label

Children's
Cold-EEZE®
Daytime
Cough & Chest
Congestion Relief

Guaifenesin 100 mg • Expectorant

Dextromethorphan HBr 5 mg • Cough Suppressant

MULTI-SYMPTOM

Relief of:

✓ Cough
✓ Breaks Up Mucus
✓ Chest Congestion

Alcohol Free
Dye Free

Cherry Flavor

For Ages 4+
6 fl oz (180 mL)

3001000215--47009

NDC 61941-0400-1